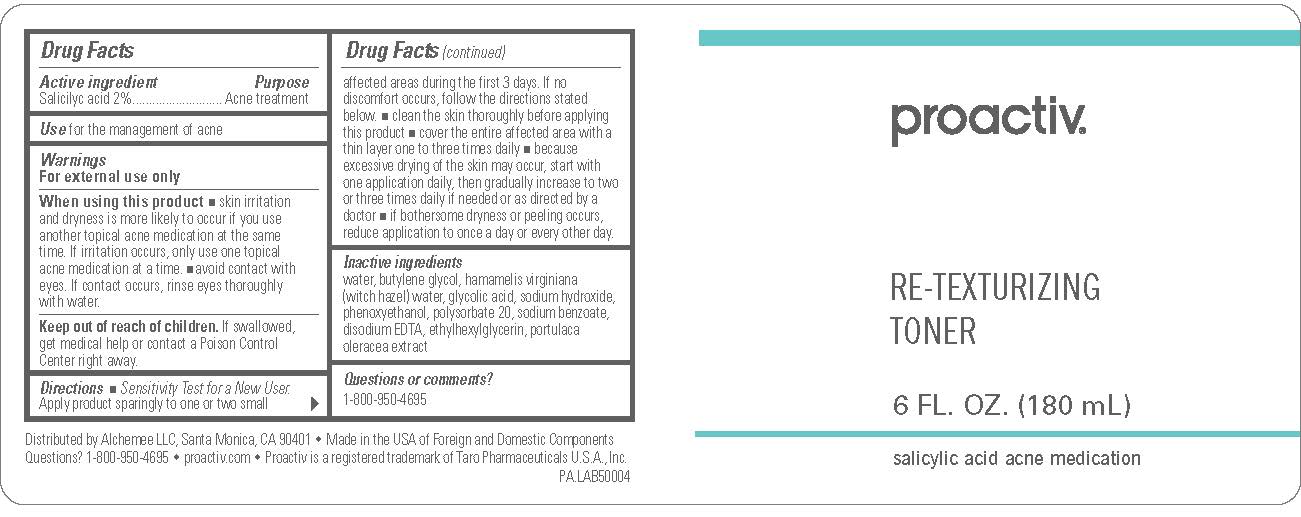 DRUG LABEL: Proactiv Plus Retexturizing Toner
NDC: 11410-051 | Form: CREAM
Manufacturer: Alchemee, LLC
Category: otc | Type: HUMAN OTC DRUG LABEL
Date: 20260107

ACTIVE INGREDIENTS: SALICYLIC ACID 20 mg/1 mL
INACTIVE INGREDIENTS: WATER; BUTYLENE GLYCOL; HAMAMELIS VIRGINIANA TOP WATER; GLYCOLIC ACID; SODIUM HYDROXIDE; PURSLANE; POLYSORBATE 20; EDETATE DISODIUM; ETHYLHEXYLGLYCERIN; SODIUM BENZOATE; PHENOXYETHANOL

Proactiv Re-texturizing Toner

Drug Facts

Active ingredients

Salicylic Acid 2%

Purpose

Acne Treatment

Use

for the management of acne

Warnings

For external use only

When using this product

- skin irritation and dryness is more likely to occur if you use another topical acne medication at the same time. If irritation occurs, only use one topical acne medication at a time.
- avoid contact with eyes. If contact occurs, rinse eyes thoroughly with water.

Keep out of reach of children.

If swallowed, get medical help or contact a Poison Control Center right away.

Directions

- Sensitivity Test for a New User. Apply product sparingly to one or two small affected areas during the first 3 days. If no discomfort occurs, follow the directions stated below.
- clean the skin thoroughly before applying this product
- cover the entire affected areas with a thin layer one to three times daily
- because excessive drying of the skin may occur, start with one application daily, then gradually increase to two or three times daily if needed or as directed by a doctor
- if bothersome dryness or peeling occurs, reduce application use to once a day or every other day.

Inactive ingredients

water, butylene glycol, hamamelis virginiana (witch hazel) water, glycolic acid, sodium hydroxide, phenoxyethanol, polysorbate 20, sodium benzoate, disodium EDTA, ethylhexylglycerin, portulaca oleracea extract

Questions or comments?

1-800-950-4695

Distributed by Alchemee LLC, Santa Monica, CA 90401 • Made in the USA of Foreign and Domestic Components Questions? 1-800-950-4695 • proactiv.com • Proactiv is a registered trademark of Taro Pharmaceuticals U.S.A., Inc.

PACKAGE LABEL.PRINCIPAL DISPLAY PANEL

Proactiv®
Re-Texturizing
Toner
6 FL. OZ. 180 mL
salicylic acid acne medication